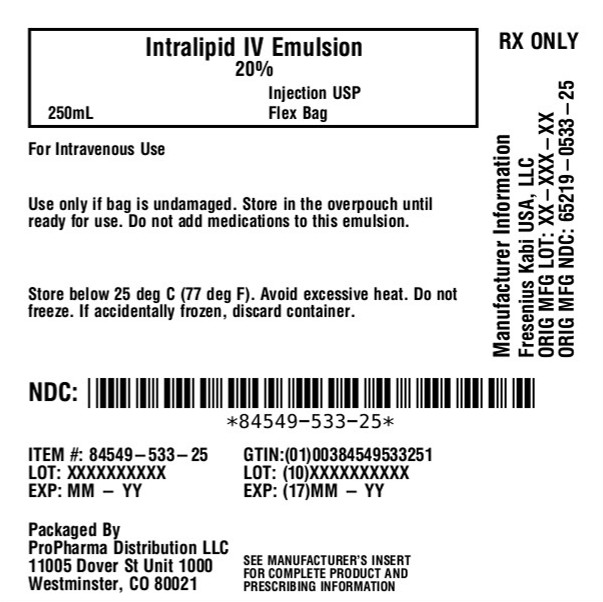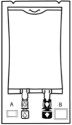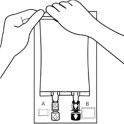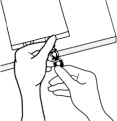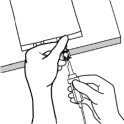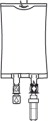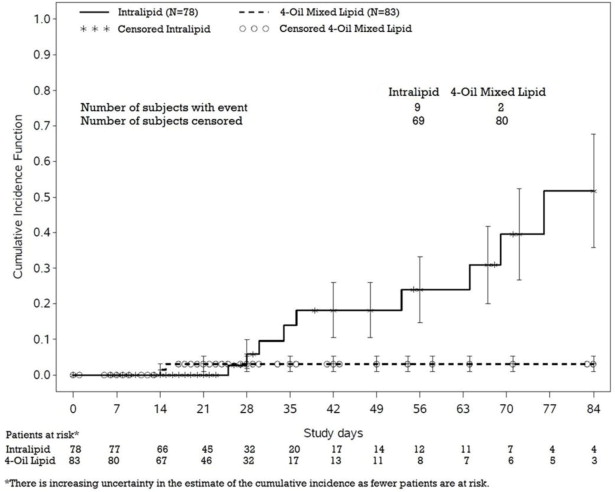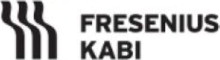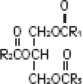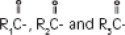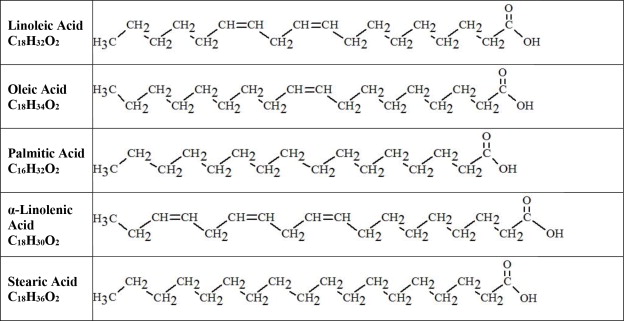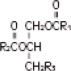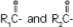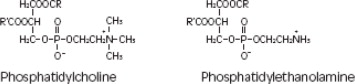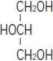 DRUG LABEL: Intralipid
NDC: 84549-533 | Form: EMULSION
Manufacturer: ProPharma Distribution
Category: prescription | Type: HUMAN PRESCRIPTION DRUG LABEL
Date: 20260119

ACTIVE INGREDIENTS: SOYBEAN OIL 20 g/100 mL
INACTIVE INGREDIENTS: EGG PHOSPHOLIPIDS; GLYCERIN; SODIUM HYDROXIDE; WATER

HIGHLIGHTS OF PRESCRIBING INFORMATION

These highlights do not include all the information needed to use INTRALIPID®safely and effectively. See full prescribing information for INTRALIPID.
INTRALIPID 20% (lipid injectable emulsion), for intravenous use
Initial U.S. Approval: 1975

RECENT MAJOR CHANGES

Warnings and Precautions (5.3) 7/2025

1 INDICATIONS AND USAGE

Intralipid is indicated as a source of calories and essential fatty acids for adult and pediatric patients requiring parenteral nutrition (PN) and as a source of essential fatty acids for prevention of essential fatty acid deficiency (EFAD).

2 DOSAGE AND ADMINISTRATION

- For intravenous infusion into a peripheral or central vein. (2.1)
- Intralipid Pharmacy Bulk Package is only indicated for use in pharmacy admixture program for the preparation of three-in-one or total nutrition admixtures (TNAs). (2.2)
- Protect the admixed PN solution from light. (2.2, 16)
- Recommended dosage depends on age, energy expenditure, clinical status, body weight, tolerance, ability to metabolize and eliminate lipids, and consideration of additional energy given to the patient. (2.3)

Age | Nutritional Requirements
Age | Initial Recommended Dosage | Maximum Dosage
Birth to 2 years of age (including preterm and term neonates) | 0.5 g/kg/day | 3 g/kg/day
Pediatric patients 2 to <12 years of age | 1 to 2 g/kg/day | 2.5 g/kg/day
Pediatric patients 12 to 17 years of age | 1 g/kg/day | 2 g/kg/day
Adults | 1 g/kg/day (stable) ≤1 g/kg/day (critically ill) | 2.5 g/kg/day

3 DOSAGE FORMS AND STRENGTHS

20% Injectable emulsion:

- 20 g/100 mL (0.2 g/mL) of lipid in 100 mL single-dose flexible container (3)
- 50 g/250 mL (0.2 g/mL) of lipid in 250 mL single-dose flexible container (3)
- 100 g/500 mL (0.2 g/mL) of lipid in 500 mL single-dose flexible container (3)
- 200 g/1,000 mL (0.2 g/mL) of lipid in 1,000 mL Pharmacy Bulk Package (3)

4 CONTRAINDICATIONS

- Known hypersensitivity to egg, soybean, or peanut, or any of the active ingredients or excipients. (4, 5.3)
- Severe disorders of lipid metabolism characterized by hypertriglyceridemia (serum triglyceride > 1,000 mg/dL). (4, 5.7)

5 WARNINGS AND PRECAUTIONS

- Risk of Clinical Decompensation with Rapid Infusion of Intravenous Lipid Emulsion in Neonates and Infants:Acute respiratory distress, metabolic acidosis, and death after rapid infusion of intravenous lipid emulsions have been reported. (5.1, 8.4)
- Risk of Parenteral Nutrition-Associated Liver Disease (PNALD):Increased risk in patients who receive PN for extended periods of time, especially preterm neonates. Monitor liver function tests; if abnormalities occur consider discontinuation or dosage reduction. (5.2, 6.1, 8.4)
- Hypersensitivity Reactions:Monitor for signs or symptoms. Discontinue infusion if reactions occur. (5.3)
- Risk of Infections, Fat Overload Syndrome, Refeeding Syndrome, and Hypertriglyceridemia:Monitor for signs and symptoms; monitor laboratory parameters. (5.4, 5.5, 5.6, 5.7)
- Aluminum Toxicity:Increased risk in patients with renal impairment, including preterm neonates. (5.8, 8.4)

6 ADVERSE REACTIONS

Most common adverse drug reactions (≥5%) from clinical trials in adults were nausea, vomiting, and pyrexia. Most common adverse drug reactions (≥5%) from clinical trials in pediatric patients were anemia, vomiting, increased gamma-glutamyltransferase, and cholestasis. (6.1)

To report SUSPECTED ADVERSE REACTIONS, contact Fresenius Kabi USA, LLC at 1-800-551-7176 or FDA at 1-800-FDA-1088 or www.fda.gov/medwatch.

7 DRUG INTERACTIONS

Vitamin K Antagonists (e.g., warfarin): Anticoagulant activity may be counteracted; increase monitoring of coagulation parameters. (7)

FULL PRESCRIBING INFORMATION

1 INDICATIONS AND USAGE

Intralipid®is indicated as a source of calories and essential fatty acids for adult and pediatric patients requiring parenteral nutrition (PN) and as a source of essential fatty acids for prevention of essential fatty acid deficiency (EFAD).

2 DOSAGE AND ADMINISTRATION

2.1 Important Administration Instructions

- Intralipid is prepared and administered by a healthcare provider in the inpatient setting. Patients and caregivers may prepare and administer Intralipid for home use after appropriate training by a trained healthcare provider.
- Intralipid is for intravenous infusion into a central or peripheral vein.
- Do not exceed the recommended maximum infusion rate in Table 1 [see Dosage and Administration (2.3) and Warnings and Precautions (5.1)].
- Intralipid admixtures with osmolarity
  - Greater than or equal to 900 mOsm/L must be infused through a central vein.
  - Less than 900 mOsm/L may be administered either through a central or peripheral vein.
- Use a 1.2 micron in-line filter during administration.
- Use a dedicated infusion line without any connections. Do not connect multiple medications in series.
- To prevent air embolism, use a non-vented infusion set or close the vent on a vented set and fully evacuate residual gas in the bag prior to administration.
- Do not pressurize the flexible bag to increase flow rates, and if administration is controlled by a pumping device, turn off the pump before the bag runs dry.
- Do not use infusion sets and lines that contain di-2-ethylhexyl phthalate (DEHP), including infusion sets that contain polyvinyl chloride (PVC) components, because they contain DEHP as a plasticizer.
- Intralipid can be infused concurrently into the same vein as dextrose-amino acid solutions (as part of PN) by a Y-connector located near the infusion site; flow rates of each solution should be controlled separately by infusion pumps.
- After connecting the infusion set, start infusion of Intralipid immediately. Complete the infusion within 12 hours when using a Y-connector and within 24 hours when used as part of an admixture.

2.2 Preparation Instructions

Use the following instructions to prepare single-dose 100 mL, 250 mL, and 500 mL Flexible containers for administration:

1. Inspect Bag

- Inspect the integrity indicator (Oxalert®) (A) before removing the overpouch.
- Discard the product if the indicator is black, overpouch is opened or damaged, emulsion color is not white, or seals of bag are broken.

2. Remove Overpouch

- Place the bag on a clean, flat surface.
- Tear the overpouch at notch and pull down.
- Discard the Oxalert sachet (A) and the oxygen absorber (B).
- Visually inspect the bag and contents for particulate matter and discoloration prior to administration. The lipid emulsion should be a homogenous liquid with a milky white appearance. If the mixture is not white or the emulsion has separated (noted by discoloration, phase separation, or oily droplets), or if particulates and/or leakage are observed, discard the bag.

3. Spike Bag

- Identify the infusion port (bluecap with the arrow pointing away from the bag).
- Immediately before inserting the infusion set, break off the blueinfusion port cap.
- Use infusion sets according to ISO Number 8536-4 with an external spike diameter of 5.5 to 5.7 mm and use a non-vented infusion set or close the air-inlet on a vented set.
- Use a 1.2 micron in-line filter for administration.
- Hold the base of the infusion port.
- Insert the spike through the infusion port by rotating your wrist slightly until the spike is inserted.
- Do not pierce the infusion port more than once.

4. Hang the bag

- On the hanger cut and start infusion.
- Discard unused portion.

Intralipid 100 mL, 250 mL, and 500 mL single-dose Flexible Containers

- After removing the overpouch, infuse immediately. If not used immediately, the product should be stored at 2°C to 8°C (36°F to 46°F) for no longer than 24 hours. After removal from storage, infuse within 12 hours when using a Y-connector and within 24 hours when used as part of an admixture.

Intralipid 1,000 mL Pharmacy Bulk Package

- For admixing use only and not for direct intravenous infusion. Prior to administration, transfer to a separate PN container for individual patient use.
- Transfer the contents through the blue infusion port using a suitable sterile transfer device or dispensing set. Discard any unused contents.
- Use the Pharmacy Bulk Package immediately for admixing after removal from the overpouch. If not used immediately, the product can be stored for no longer than 24 hours at 2°C to 8°C (36°F to 46°F). After removal from storage, and once the closure is penetrated, use Pharmacy Bulk Package contents within 4 hours.

Admixing Instructions

- Prepare the admixture in PN containers using strict aseptic techniques to avoid microbial contamination.
- Do not add Intralipid to the PN container first; destabilization of the lipid may occur. The prime destabilizers of emulsions are excessive acidity (such as a pH <5) and inappropriate electrolyte content. Amino acid solutions exert buffering effects that protect the emulsion from destabilization. Give careful consideration to the addition of divalent cations (Ca++ and Mg++), which have been shown to cause emulsion instability.
- Do not inject additives directly into Intralipid.
- Intralipid may be mixed with amino acid and dextrose injections to produce “all-in-one” PN admixtures. The mixing sequence below must be followed for manual compounding to minimize pH-related problems by ensuring that typically acidic dextrose injections are not mixed with lipid emulsions alone; shake bags gently after each addition.
  - Transfer dextrose injection to the PN container.
  - Transfer amino acid injection.
  - Transfer Intralipid.
- Simultaneous transfer of amino acid injection, dextrose injection, and Intralipid to the PN container is also permitted; follow automated compounding device instructions as indicated. Use gentle agitation during admixing to minimize localized concentration effects.
- Additions to the PN admixtures should be evaluated by a pharmacist for compatibility. Questions about compatibility may be directed to Baxter Healthcare.
- Inspect the admixture to ensure that precipitates have not formed during preparation of the admixture and the emulsion has not separated. Discard the admixture if any of the above are observed.
- Infuse admixtures containing Intralipid immediately. If not used immediately, store admixtures under refrigeration at 2°C to 8°C (36°F to 46°F) for no longer than 24 hours. Infusion must be complete within 24 hours after removal from refrigeration. Discard any remaining admixture.
- Protect the admixed PN solution from light.

2.3 Recommended Dosage and Administration

- The recommended nutritional requirements of lipid and recommended dosages of Intralipid to be administered to meet those requirements for adults and pediatric patients are provided in Table 1, along with recommendations for the initial and maximum infusion rates.
- The dosing of Intralipid depends on the patient's individual energy requirements influenced by age, body weight, tolerance, clinical status, and the ability to metabolize and eliminate lipids.
- When determining dose, energy supplied by dextrose and amino acids from PN, as well as energy from oral or enteral nutrition, has to be taken into account. Energy and lipid provided from lipid-based medications should also be taken into account (e.g., propofol).
- Prior to administration of Intralipid, correct severe fluid and electrolyte disorders and measure serum triglyceride levels to establish a baseline value. In patients with elevated triglyceride levels, initiate Intralipid at a lower dosage and titrate in smaller increments, monitoring the triglyceride levels with each adjustment [see Warnings and Precautions (5.7)] .

Table 1: Recommended Pediatric and Adult Dosage and Infusion Rate
Age | Nutritional Requirements | Direct Infusion Rate
 | Recommended Initial Dosage and Maximum Dosage | Initial | Maximum
Birth to 2 years of age (including preterm and term neonates*) [see Warnings and Precautions (5.1)] | Initial 0.5 g/kg/day not to exceed 3 g/kg/day** | 0.1 mL/kg/hour for the first 10 to 15 minutes; gradually increase to the required rate after 15 minutes | 0.75 mL/kg/hour
Pediatric patients 2 to <12 years of age | Initial 1 to 2 g/kg/day not to exceed 2.5 g/kg/day*** | 0.2 to 0.4 mL/kg/hour for the first 10 to 15 minutes; gradually increase to the required rate after 15 minutes | 0.75 mL/kg/hour
Pediatric patients 12 to 17 years of age | Initial 1 g/kg/day not to exceed 2 g/kg/day** | 0.2 mL/kg/hour for the first 10 to 15 minutes; gradually increase to the required rate after 15 minutes | 0.75 mL/kg/hour
Adults | 1 g/kg/day in stable patients ≤1 g/kg/day in critically ill patients not to exceed 2.5 g/kg/day; not more than 500 mL of Intralipid should be infused on the first day of therapy** | 0.2 mL/kg/hour for the first 10 to 15 minutes; gradually increase to the required rate after 30 minutes | 0.5 mL/kg/hour
* The neonatal period is defined as including term, post-term, and preterm neonates. The neonatal period for term and post-term neonates is the day of birth plus 27 days. For preterm neonates, the neonatal period is defined as the day of birth through the expected age of delivery plus 27 days (i.e., 44 weeks post-menstrual age).
** Daily dosage should also not exceed a maximum of 60% of total energy requirements [see Overdosage (10)].

Dosage Modifications in Patients with Essential Fatty Acid Deficiency

When Intralipid is administered to correct essential fatty acid deficiency (EFAD), supply 8% to 10% of caloric input from Intralipid in order to provide adequate amounts of linoleic and linolenic acids.

3 DOSAGE FORMS AND STRENGTHS

Intralipid 20% is a sterile, homogenous, milky, white lipid injectable emulsion in Flexible Containers supplied as:

- 20 g/100 mL (0.2 g/mL) of lipid in 100 mL single-dose Flexible Container
- 50 g /250 mL (0.2 g/mL) of lipid in 250 mL single-dose Flexible Container
- 100 g/500 mL (0.2 g/mL) of lipid in 500 mL single-dose Flexible Container
- 200 g /1,000 mL (0.2 g/mL) of lipid in 1,000 mL Pharmacy Bulk Package

4 CONTRAINDICATIONS

- Known hypersensitivity to egg, soybean, peanut, or any of the active or inactive ingredients in Intralipid [see Warnings and Precautions (5.3)]
- Severe disorders of lipid metabolism characterized by hypertriglyceridemia (serum triglyceride > 1,000 mg/dL) [see Warnings and Precautions (5.7)]

5 WARNINGS AND PRECAUTIONS

5.1 Clinical Decompensation with Rapid Infusion of Intravenous Lipid Emulsions in Neonates and Infants

In the postmarketing setting, serious adverse reactions including acute respiratory distress, metabolic acidosis, and death have been reported in neonates and infants after rapid infusion of intravenous lipid emulsions. Hypertriglyceridemia was commonly reported.

Strictly adhere to the recommended total daily dosage; the hourly infusion rate should not exceed 0.75 mL/kg/hour [see Dosage and Administration (2.3)].

Preterm and small for gestational age infants have poor clearance of intravenous lipid emulsion and increased free fatty acid plasma levels following lipid emulsion infusion.

Carefully monitor the infant's ability to eliminate the infused lipids from the circulation (e.g., measure serum triglycerides and/or plasma free fatty acid levels). If signs or poor clearance of lipids from the circulation occur, stop the infusion and initiate a medical evaluation [see Warnings and Precautions (5.5, 5.7) and Overdosage (10)].

5.2 Parenteral Nutrition-Associated Liver Disease and Other Hepatobiliary Disorders

Risk of Parenteral Nutrition-Associated Liver Disease

Parenteral nutrition-associated liver disease (PNALD), also referred to as intestinal failure- associated liver disease (IFALD), can present as cholestasis or hepatic steatosis, and may progress to steatohepatitis with fibrosis and cirrhosis (possibly leading to chronic hepatic failure). The etiology of PNALD is multifactorial; however, intravenously administered phytosterols (plant sterols) contained in plant-derived lipid emulsions, including Intralipid, have been associated with development of PNALD.

In a randomized study of neonates and infants expected to be treated with PN for at least 28 days, parenteral nutrition-associated cholestasis (PNAC), a precursor to PNALD, developed more frequently in Intralipid-treated patients than patients treated with a 4-oil mixed lipid emulsion. [see Adverse Reactions (6.1), Use in Specific Populations (8.4)] .

Monitor liver tests in patients treated with Intralipid and consider discontinuation or dosage reduction if abnormalities occur.

Other Hepatobiliary Disorders

Hepatobiliary disorders including cholecystitis and cholelithiasis have developed in some PN-treated patients without preexisting liver disease.

Monitor liver tests when administering Intralipid. Patients developing signs of hepatobiliary disorders should be assessed early to determine whether these conditions are related to Intralipid use.

5.3 Hypersensitivity Reactions

Intralipid contains soybean oil and egg phospholipids, which may cause hypersensitivity reactions. Cross reactions have been observed between soybean and peanut. In postmarketing experience, anaphylaxis has been reported following Intralipid administration [see Adverse Reactions (6.2)] .

Intralipid is contraindicated in patients with known hypersensitivity to egg, soybean, peanut or any of the active or inactive ingredients in Intralipid [see Contraindications (4)] . If a hypersensitivity reaction occurs, stop infusion of Intralipid immediately and initiate appropriate treatment and supportive measures.

5.4 Infections

Parenteral nutrition, such as Intralipid, can support microbial growth and is an independent risk factor for the development of catheter-related bloodstream infections. To decrease the risk of infectious complications, ensure aseptic techniques are used for catheter placement, catheter maintenance, and preparation and administration of Intralipid.

Monitor for signs and symptoms of infection including fever and chills, as well as laboratory test results that might indicate infection (including leukocytosis and hyperglycemia). Perform frequent checks of the intravenous catheter insertion site for edema, redness, and discharge.

5.5 Fat Overload Syndrome

Fat overload syndrome is a rare condition that has been reported with intravenous lipid injectable emulsions and is characterized by a sudden deterioration in the patient's condition (e.g., fever, anemia, leukopenia, thrombocytopenia, coagulation disorders, hyperlipidemia, hepatomegaly, deteriorating liver function, and central nervous system manifestations such as coma). A reduced or limited ability to metabolize lipids, accompanied by prolonged plasma clearance (resulting in higher lipid levels), may result in this syndrome. Although fat overload syndrome has been most frequently observed when the recommended lipid dose or infusion rate was exceeded, cases have also been described when the lipid formulation was administered according to instructions.

If signs or symptoms of fat overload syndrome occur, stop the infusion of Intralipid. The syndrome is usually reversible when the infusion of the lipid emulsion is stopped.

5.6 Refeeding Syndrome

Administering PN to severely malnourished patients may result in refeeding syndrome, which is characterized by the intracellular shift of potassium, phosphorus, and magnesium as patients become anabolic. Thiamine deficiency and fluid retention may also develop. To prevent these complications, closely monitor severely malnourished patients and slowly increase their nutrient intake.

5.7 Hypertriglyceridemia

The use of Intralipid is contraindicated in patients with hypertriglyceridemia with serum triglyceride concentrations >1,000 mg/dL.

Patients with conditions such as inherited lipid disorders, obesity, diabetes mellitus, or metabolic syndromes have a higher risk of developing hypertriglyceridemia with the use of Intralipid. In addition, patients with hypertriglyceridemia may have worsening of their hypertriglyceridemia with administration of Intralipid. Excessive dextrose administration may further increase such risk.

Evaluate patients' capacity to metabolize and eliminate the infused lipid emulsion by measuring serum triglycerides before the start of infusion (baseline value) and regularly throughout treatment. If triglyceride levels are above 400 mg/dL in adults, stop the Intralipid infusion and monitor serum triglyceride levels to avoid clinical consequences of hypertriglyceridemia such as pancreatitis. In pediatric patients with hypertriglyceridemia, lower triglyceride levels (i.e., below 400 mg/dL) may be associated with adverse reactions. Monitor serum triglyceride levels to avoid potential complications with hypertriglyceridemia such as pancreatitis, lipid pneumonitis, and neurologic changes, including kernicterus.

To minimize the risk of new or worsening of hypertriglyceridemia, assess high-risk patients for their overall energy intake including other sources of lipids and dextrose, as well as concomitant drugs that may affect lipid and dextrose metabolism.

5.8 Aluminum Toxicity

Intralipid contains no more than 25 mcg/L of aluminum. Prolonged PN administration in patients with renal impairment may result in aluminum reaching toxic levels. Preterm neonates are at greater risk because their kidneys are immature, and they require large amounts of calcium and phosphate solutions that contain aluminum.

Patients with impaired kidney function, including preterm neonates, who receive parenteral levels of aluminum at greater than 4 to 5 mcg/kg/day can accumulate aluminum at levels associated with central nervous system and bone toxicity. Tissue loading in these patients may occur at even lower rates of administration.

5.9 Monitoring/Laboratory Tests

Monitor fluid status closely in patients with pulmonary edema or heart failure.

Throughout treatment, monitor serum triglycerides [see Warnings and Precautions (5.7)], essential fatty acids, fluid and electrolyte status, serum osmolarity, blood glucose, liver and kidney function, blood count (including platelets), and coagulation parameters.

The lipids contained in Intralipid may interfere with some laboratory tests (e.g., hemoglobin, lactate dehydrogenase, bilirubin, oxygen saturation) if blood is sampled before lipids have cleared from the bloodstream. Conduct these tests at least 6 hours after stopping the infusion.

Intralipid contains vitamin K that may counteract anticoagulant activity [see Drug Interactions (7)] .

6 ADVERSE REACTIONS

Adverse reactions described elsewhere in this Prescribing Information are:

- Clinical Decompensation with Rapid Infusion of Intravenous Lipid Emulsion in Neonates and Infants [see Warnings and Precautions (5.1)]
- Parenteral Nutrition-Associated Liver Disease and Other Hepatobiliary Disorders [see Warnings and Precautions (5.2)]
- Hypersensitivity Reactions [see Warnings and Precautions (5.3)]
- Infections [see Warnings and Precautions (5.4)]
- Fat Overload Syndrome [see Warnings and Precautions (5.5)]
- Refeeding Syndrome [see Warnings and Precautions (5.6)]
- Hypertriglyceridemia [see Warnings and Precautions (5.7)]
- Aluminum Toxicity [see Warnings and Precautions (5.8)]

6.1 Clinical Trials Experience

Because clinical trials are conducted under widely varying conditions, adverse reaction rates observed in the clinical trials of a drug cannot be compared to rates in the clinical trials of another drug and may not reflect the rates observed in clinical practice.

Intralipid or equivalent soybean oil lipid emulsions functioned as the comparator in trials of the 4-oil mixed lipid emulsion [see Clinical Studies (14)]. The adverse reactions from these studies are included to present the clinical experience with Intralipid.

The safety database for Intralipid or equivalent soybean oil lipid emulsion exposure in these studies includes 393 patients (230 adults; 163 pediatric) in 9 clinical trials. Adult patients were exposed for 5 days to 4 weeks in 5 clinical trials. Intralipid or equivalent soybean oil lipid emulsion was used as a component of PN which also included dextrose, amino acids, vitamins, and trace elements. Two of the 5 studies in adults were performed with Intralipid as a component of PN delivered in a 3-chamber bag.

Table 2: Adverse Reactions in >1% of Adult Patients Treated with Intralipid/Soybean oil emulsion
Adverse Reaction | Number of Patients in Soybean Oil Lipid Emulsion Group (N=230) | Number of Patients in 4-Oil Mixed Lipid Emulsion Comparator Group (N=229)
Nausea | 26 (11%) | 20 (9%)
Vomiting | 12 (5%) | 15 (7%)
Pyrexia | 11 (5%) | 9 (4%)
Hypertension | 9 (4%) | 6 (3%)
Headache | 7 (3%) | 3 (1%)
Hyperglycemia | 5 (2%) | 12 (5%)
Abdominal pain | 5 (2%) | 8 (4%)
Flatulence | 4 (2%) | 10 (4%)
Blood triglycerides increased | 4 (2%) | 6 (3%)
Sepsis | 4 (2%) | 5 (2%)
Diarrhea | 4 (2%) | 3 (1%)
Pneumonia | 4 (2%) | 3 (1%)
Pruritus | 4 (2%) | 3 (1%)
Gamma-glutamyltransferase increased | 4 (2%) | 2 (1%)

Less common adverse reactions occurring in ≤1% of adult patients who received Intralipid or equivalent soybean oil lipid emulsion were dyspepsia, urinary tract infection, anemia, infection, dyspnea, cholestasis, dysgeusia, increased blood alkaline phosphatase, tachycardia, liver function test abnormalities, dizziness, rash, and thrombophlebitis.

The 163 patients treated with Intralipid in four pediatric trials consisted of 147 patients <28 days of age, 9 patients 28 days to <2 years of age, and 7 patients 2 to 7 years of age; the duration of exposure was 7 to 84 days. Fifty-six percent of the pediatric patients were female, and 85% were Caucasian. Most pediatric patients were preterm neonates with feeding intolerance or other conditions requiring short-term (<29 days) PN.

Table 3: Adverse Reactions in >1% of Pediatric Patients Treated with Intralipid
Adverse Reaction | Number of Patients in Intralipid Group (N=163) | Number of Patients in 4-Oil Mixed Lipid Emulsion Comparator Group (N=170)
Anemia | 33 (20%) | 30 (18%)
Vomiting | 16 (10%) | 16 (9%)
Gamma-glutamyltransferase increased | 12 (7%) | 10 (6%)
Cholestasis | 10 (6%) | 7 (4%)
Pyrexia | 7 (4%) | 7 (4%)
C-reactive protein increased | 7 (4%) | 6 (4%)
Hyperbilirubinemia | 7 (4%) | 5 (3%)
Bilirubin conjugated increased | 7 (4%) | 3 (2%)
Nosocomial infection | 6 (4%) | 10 (6%)
Blood alkaline phosphatase increased | 6 (4%) | 1 (1%)
Abdominal pain | 5 (3%) | 4 (2%)
Hematocrit decreased | 5 (3%) | 2 (1%)
Metabolic acidosis | 5 (3%) | 2 (1%)
Diarrhea | 4 (3%) | 3 (2%)
Tachycardia | 4 (3%) | 3 (2%)
Thrombocytopenia | 4 (3%) | 3 (2%)
Alanine aminotransferase increased | 3 (2%) | 1 (1%)
Aspartate aminotransferase increased | 3 (2%) | 0 (0%)
Parenteral nutrition-associated liver disease | 3 (2%) | 0 (0%)

Less common adverse reactions occurring in ≤1% of pediatric patients who received Intralipid were hyperglycemia, sepsis, increased blood triglycerides, infection, fluid overload, hypertension, hypertriglyceridemia, rash, and hyperlipidemia.

In a randomized active-controlled, double-blind, parallel-group, multi-center study that included 152 neonates and 9 patients ranging in age from 29 to 153 days who were expected to require PN for at least 28 days, PNAC, a precursor to PNALD, developed more frequently in Intralipid-treated patients than in patients treated with a comparator 4-oil mixed lipid emulsion.

PNAC (defined as direct bilirubin >2 mg/dL with a second confirmed elevation >2 mg/dL at least 7 days later) occurred in 11.5% (9/78) in Intralipid-treated patients and 2.4% (2/83) of patients treated with a 4-oil mixed lipid emulsion. Most PNAC events occurred in patients who were treated for longer than 28 days.

The estimated cumulative incidence of PNAC is shown in the Kaplan-Meier cumulative incidence curve in Figure 1 [see Pediatric Clinical Studies (14.2)] .

Figure 1: Cumulative Incidence Curve of Time to Parenteral Nutrition-Associated Cholestasis (PNAC) with Standard Error Bars

6.2 Postmarketing Experience

The following adverse reactions from voluntary reports have been reported with Intralipid. Because many of these reactions were reported voluntarily from a population of uncertain size, it is not always possible to reliably estimate their frequency or establish a causal relationship to drug exposure.

Cardiac disorders:palpitations
Gastrointestinal disorders:vomiting, nausea
General disorders and administration site conditions:chills, chest discomfort, pyrexia
Nervous system disorders:dizziness
Respiratory, thoracic, and mediastinal disorders: dyspnea
Immune system disorders:hypersensitivity reactions, including anaphylaxis [see Contraindications (4), Warnings and Precautions (5.3)]
Vascular disorders: phlebitis
Blood and lymphatic system disorders:hypercoagulability

7 DRUG INTERACTIONS

Soybean oil in Intralipid contains vitamin K1which may counteract the anticoagulant activity of vitamin K antagonists such as warfarin. In patients who receive concomitant Intralipid and warfarin, increase monitoring of laboratory parameters for anticoagulant activity.

8 USE IN SPECIFIC POPULATIONS

8.1 Pregnancy

Risk Summary

Administration of the recommended dose of Intralipid is not expected to cause major birth defects, miscarriage, or other adverse maternal or fetal outcomes. No animal reproduction studies have been conducted with Intralipid. There are risks to the fetus associated with severe malnutrition during pregnancy (see Clinical Considerations) .

The background risk of major birth defects and miscarriage for the indicated population(s) is unknown. All pregnancies have a background risk of birth defect, loss, or other adverse outcomes. In the U.S. general population, the estimated background risk of major birth defects and miscarriage in clinically recognized pregnancies is 2% to 4% and 15% to 20%, respectively.

Clinical Considerations

Disease-Associated Maternal and/or Embryo-Fetal Risk

Severe malnutrition in pregnant women is associated with preterm delivery, low birth weight, intrauterine growth restriction, congenital malformations, and perinatal mortality. Parenteral nutrition should be considered if the pregnant woman's nutritional requirements cannot be fulfilled by oral or enteral intake.

8.2 Lactation

Risk Summary

Administration of the recommended dose of Intralipid is not expected to cause harm to a breastfed infant. There are no data on the presence of Intralipid in human or animal milk or its effects on milk production. Available published literature includes fewer than five reported cases of breastfed infants exposed to various lipid emulsions via lactation, and these cases did not report adverse events. The developmental and health benefits of breastfeeding should be considered along with the mother's clinical need for Intralipid and any potential adverse effects of Intralipid on the breastfed infant, or from the underlying maternal condition.

8.4 Pediatric Use

Intralipid is contraindicated in pediatric patients with severe disorders of lipid metabolism [ (see Contraindications (4)].

The safety and effectiveness of Intralipid have been established as a source of calories and essential fatty acids for PN in pediatric patients, including term and preterm neonates. Use of Intralipid in neonates is supported by evidence from short-term (i.e., 1- to 4- week) studies, and one study following neonates beyond 4 weeks [see Clinical Studies (14.2)] . Use of Intralipid in older pediatric patients is supported by evidence from short-term (i.e., <28 days) studies in pediatric patients 28 days to 12 years of age and additional evidence from studies in adults [see Clinical Studies (14)] . The most common adverse reactions in Intralipid-treated pediatric patients were anemia, vomiting, gamma-glutamyltransferase increased, and cholestasis. PNAC, a precursor to PNALD, developed more frequently in Intralipid-treated patients than in patients treated with a comparator 4-oil mixed lipid emulsion [see Warnings and Precautions (5.1) and Adverse Reactions (6.1)].

In the postmarketing setting, clinical decompensation with rapid infusion of intravenous lipid emulsion in neonates and infants, sometimes fatal, has been reported [see Warnings and Precautions (5.1)] . Because of immature renal function, preterm neonates receiving prolonged treatment with Intralipid may be at risk for aluminum toxicity [see Warnings and Precautions (5.8)] .

8.5 Geriatric Use

Reported clinical experience has not identified differences in responses between the elderly and younger patients. In general, dose selection for an elderly patient should be cautious, usually starting at the low end of the dosing range, reflecting the greater frequency of decreased hepatic, renal, or cardiac function, and of concomitant disease or drug therapy.

10 OVERDOSAGE

In the event of an overdose, serious adverse reactions may result [see Warnings and Precautions (5.1, 5.5)] . Stop the infusion of Intralipid until triglyceride levels have normalized and symptoms have abated. The effects are usually reversible by stopping the lipid infusion. If medically appropriate, further intervention may be indicated. Lipids are not dialyzable from plasma.

11 DESCRIPTION

Intralipid is a sterile, non-pyrogenic, white, homogenous lipid emulsion for intravenous infusion as a source of calories and essential fatty acids. The lipid content of Intralipid is 0.2 g/mL and comprises soybean oil. The phosphate content is 15 mmol/L.

The total energy content, including fat, phospholipids, and glycerin is 2,000 kcal/L.

Each 100 mL of Intralipid contains approximately 20 g soybean oil, 1.2 g egg yolk phospholipids, 2.25 g glycerin, water for injection, and sodium hydroxide for pH adjustment (pH 6 to 8.9). Intralipid has an osmolality of approximately 350 mOsmol/kg water (which represents an osmolarity of 260 mOsmoL/L).

The soybean oil is a refined natural product consisting of a mixture of neutral triglycerides of predominantly unsaturated fatty acids with the following structure:

where are saturated and unsaturated fatty acid residues.

The major component fatty acids in Intralipid are linoleic acid (44% to 62%), oleic acid (19% to 30%), palmitic acid (7% to 14%), alpha-linolenic acid (4% to 11%), and stearic acid (1.4% to 5.5%). These fatty acids have the following chemical and structural formulas:

Purified egg phosphatides are a mixture of naturally occurring phospholipids which are isolated from the egg yolk. These phospholipids have the following general structure:

contain saturated and unsaturated fatty acids that abound in neutral fats. R3is primarily either the choline or ethanolamine ester of phosphoric acid.

Glycerin is chemically designated C3H8O3and is a clear colorless, hygroscopic syrupy liquid. It has the following structural formula:

The container-solution unit is a closed system and is not dependent upon entry of external air during administration. The container is overwrapped to provide protection from the physical environment and to provide an additional oxygen and moisture barrier when necessary.

Intralipid contains no more than 25 mcg/L of aluminum.

The container is not made with natural rubber latex, PVC, or DEHP.

12 CLINICAL PHARMACOLOGY

12.1 Mechanism of Action

Intralipid provides a biologically utilizable source of calories and essential fatty acids.

Fatty acids serve as an important substrate for energy production. The most common mechanism of action for energy production derived from fatty acid metabolism is beta oxidation. Fatty acids are also important for membrane structure and function, as precursors for bioactive molecules (such as prostaglandins), and as regulators of gene expression.

12.2 Pharmacodynamics

The pharmacodynamic effects of Intralipid have not been fully characterized.

12.3 Pharmacokinetics

Intralipid provides fatty acids in the form of triglycerides which are hydrolyzed by lipoprotein lipase to release free fatty acids. Linoleic acid and alpha-linolenic acid are metabolized within a common biochemical pathway through a series of desaturation and elongation steps.

13 NONCLINICAL TOXICOLOGY

13.1 Carcinogenesis, Mutagenesis, Impairment of Fertility

Carcinogenicity, genetic toxicology, and animal fertility studies have not been performed with Intralipid.

14 CLINICAL STUDIES

Intralipid or equivalent soybean oil lipid emulsion functioned as the comparator for the 4-oil mixed lipid emulsion in the clinical studies described in sections 14.1 and 14.2. The trial results are included to present the clinical experience with Intralipid.

14.1 Adult Clinical Studies

The efficacy of Intralipid or equivalent soybean oil lipid emulsion compared to a 4-oil mixed lipid emulsion was evaluated in 3 clinical studies in adult patients. Nutritional efficacy in adult studies was assessed by changes in anthropometric indices (body weight, height, and body mass index [BMI]), changes in lipid and protein metabolism (albumin), and fatty acid parameters. Of the 354 adult patients (178 Intralipid; 176 comparator), 62% were male, 99% were Caucasian, and ages ranged from 19 to 96 years. All patients received Intralipid/equivalent soybean oil lipid emulsion or the comparator as part of a PN regimen. Although Adult Study 1, Adult Study 2, and Adult Study 3 were not designed for formal statistical comparisons between Intralipid/equivalent soybean oil lipid emulsion and the comparator, they support Intralipid as a source of calories and essential fatty acids in adults. The lipid dosage was variable in these studies and adjusted to the patient's nutritional requirements.

Adult Study 1 was a double-blind, randomized, active-controlled, parallel-group, multicenter study in patients who required PN for at least 28 days. Seventy-five patients were enrolled, and 73 patients were treated with either Intralipid or the comparator. Changes in mean triglyceride levels from baseline values to Week 4 were similar in both the Intralipid and comparator groups. Mean albumin levels demonstrated a comparable decrease in both groups. Mean changes in body weight (kg) and BMI (kg/m^2) were similar in both the Intralipid and the comparator groups.

Adult Study 2 was a phase 3, randomized, double-blind, active-controlled, multicenter study. A total of 249 postoperative adult patients were randomized to receive either an equivalent soybean oil lipid emulsion to Intralipid or the comparator for at least 5 days as part of their total parenteral nutrition (TPN) regimen. From baseline to Day 6, mean triglyceride levels increased similarly in both the soybean oil lipid emulsion and the comparator groups.

Adult Study 3 was a double-blind randomized, active-controlled, parallel-group, single-center study in 32 adult patients who required TPN for 10 to 14 days. Patients were treated with either an equivalent soybean oil lipid emulsion to Intralipid or the comparator. The increase in mean triglyceride levels from baseline to the final assessment was similar in both the soybean oil lipid emulsion and the comparator groups.

14.2 Pediatric Clinical Studies

The efficacy of Intralipid compared to a 4-oil mixed lipid emulsion in pediatric patients of all age groups, including term and preterm neonates, was evaluated in 333 patients in 4 randomized active-controlled, double-blind, parallel-group controlled clinical studies. Although Pediatric Studies 1, 2, 3, and 4 were not designed for formal statistical comparisons between Intralipid and the comparator, they support Intralipid as a source of calories and essential fatty acids in pediatric patients. The 333 pediatric patients (163 Intralipid; 170 comparator) consisted of 296 patients who were <28 days old, 22 patients 29 days to <2 years old, and 15 patients 2 to <12 years old. Fifty percent of the pediatric patients were male and 87% were Caucasian. All patients received Intralipid or the comparator as part of a PN regimen. Nutritional efficacy in neonates was assessed by changes in anthropometric indices (body weight, height, head circumference). Nutritional efficacy in pediatric patients, 28 days to 12 years of age, was assessed by changes in triglyceride concentrations and fatty acid parameters.

Pediatric Study 1 enrolled 152 preterm and term neonates (birth up to 28 days) and 9 patients ranging in age from 29 to 153 days. Patients were treated with either Intralipid (n=78) or the comparator (n=83). A total of 119 patients (58 Intralipid; 61 comparator) received study treatment for ≥14 days. A total of 27 patients received Intralipid for ≥29 days; 5 patients received Intralipid for the maximum study duration of 78-84 days.

Pediatric Studies 2 and 3 enrolled 60 and 84 preterm neonates, respectively, who were treated with either Intralipid or the comparator (72 neonates in each group). The median treatment duration for Intralipid group was 9 days in Pediatric Study 2 and 6 days in Pediatric Study 3.

Pediatric Study 4 enrolled 13 patients 5 months to <2 years of age and 15 patients 2 to 11.5 years of age. Patients were treated with either Intralipid (n=13) or the comparator (n=15) with a median treatment duration of 27 days.

In Pediatric Studies 1, 2 and 3, which enrolled neonates, Intralipid-treated patients showed increases in the median body weight, height/length, and head circumference (which was measured in Studies 1 and 3) comparable to the comparator-treated patients. Mean triglyceride levels from baseline to the final assessment in Pediatric Studies 1, 2, and 3 were variable in these neonates, but overall differences between groups were not considered clinically relevant. Mean triglyceride levels in Pediatric Study 4 were variable but remained within the normal range.

16 HOW SUPPLIED/STORAGE AND HANDLING

Intralipid 20% (lipid injectable emulsion, USP) is a sterile, homogeneous, milky, white lipid emulsion supplied in Flexible Containers as follows:

Unit

NDC 84549-533-25
One 250 mL
freeflex®bag

Store below 25°C (77°F). Avoid excessive heat. Do not freeze. If accidentally frozen, discard container. Store in the overpouch until ready for use.

Intralipid 250 mL single-dose Flexible Containers

After removing the overpouch, infuse immediately. If not used immediately, the product should be stored at 2°C to 8°C (36°F to 46°F) for no longer than 24 hours. After removal from storage, infuse within 12 hours when using a Y-connector or within 24 hours if used as part of an admixture [see Dosage and Administration (2.2)].

Admixtures

Infuse admixtures containing Intralipid immediately. If not used immediately, admixtures should be stored at 2°C to 8°C (36°F to 46°F) for no longer than 24 hours. After removal from storage, infuse within 24 hours [see Dosage and Administration (2.2)] .

Protect the admixed PN solution from light [see Dosage and Administration (2.2)].

17 PATIENT COUNSELING INFORMATION

When initiating Intralipid administration, discuss the following information with the patient or caregiver:

Clinical Decompensation with Rapid Infusion of Intravenous Lipid Emulsion in Neonates and Infants

Inform caregivers that acute respiratory distress and death may occur in neonates and infants after rapid infusion of intravenous lipid emulsions. If Intralipid is infused at home, instruct caregivers not to exceed the maximum infusion rate [see Warnings and Precautions (5.1)].

Parenteral Nutrition-Associated Liver Disease and Other Hepatobiliary Disorders

Inform patients and caregivers that use of parenteral nutrition may result in parenteral nutrition- associated liver disease and/or other hepatobiliary disorders [see Warnings and Precautions (5.2)].

Hypersensitivity Reactions

Inform patients and caregivers that Intralipid may cause hypersensitivity reactions, including anaphylaxis. If Intralipid is infused at home, instruct patients or caregivers to stop the infusion of Intralipid immediately and seek medical attention if they experience signs or symptoms of a hypersensitivity reaction, such as rapid or weak heartbeat, feeling faint, difficulty in breathing or swallowing, vomiting, nausea, headache, sweating, dizziness, hives, rash, itching, flushing, dizziness, fever, or chills [see Warnings and Precautions (5.3)].

Infections

Inform patients and caregivers that patients who receive Intralipid are at risk of infection. If Intralipid is infused at home, instruct patients or caregivers to ensure aseptic techniques are used for the preparation and administration of Intralipid and to monitor for signs and symptoms of infection [see Warnings and Precautions (5.4)] .

Fat Overload Syndrome

Inform patients and caregivers that fat overload syndrome has been reported with the use of intravenous lipid emulsions. If Intralipid is infused at home, instruct patients or caregivers to stop the infusion of Intralipid if signs or symptoms of fat overload syndrome occur [see Warnings and Precautions (5.5)] .

Refeeding Syndrome

If the patient is severely malnourished, inform patients and caregivers that administering parenteral nutrition including Intralipid may result in refeeding syndrome [see Warnings and Precautions (5.6)] .

Hypertriglyceridemia

Inform patients and their caregivers about the risks of hypertriglyceridemia with Intralipid use [see Warnings and Precautions (5.7)] .

Aluminum Toxicity

Inform patients and their caregivers that prolonged PN administration in patients with renal impairment, including preterm neonates, may result in aluminum reaching toxic levels associated with central nervous system and bone toxicity [see Warnings and Precautions (5.8)] .

Preparation and Administration Instructions

If it is acceptable for a patient or caregiver to administer Intralipid at home, then provide recommendations on how to inspect and prepare, add compatible additives (when appropriate), administer, and store Intralipid [see Dosage and Administration (2.1, 2.2)] . Inform patients or caregivers not to deviate from the administration instructions given by the healthcare provider.

Manufactured by:

Uppsala, Sweden

Intralipid®is a registered trademark of Fresenius Kabi AB.
www.fresenius-kabi.com/us
451713C